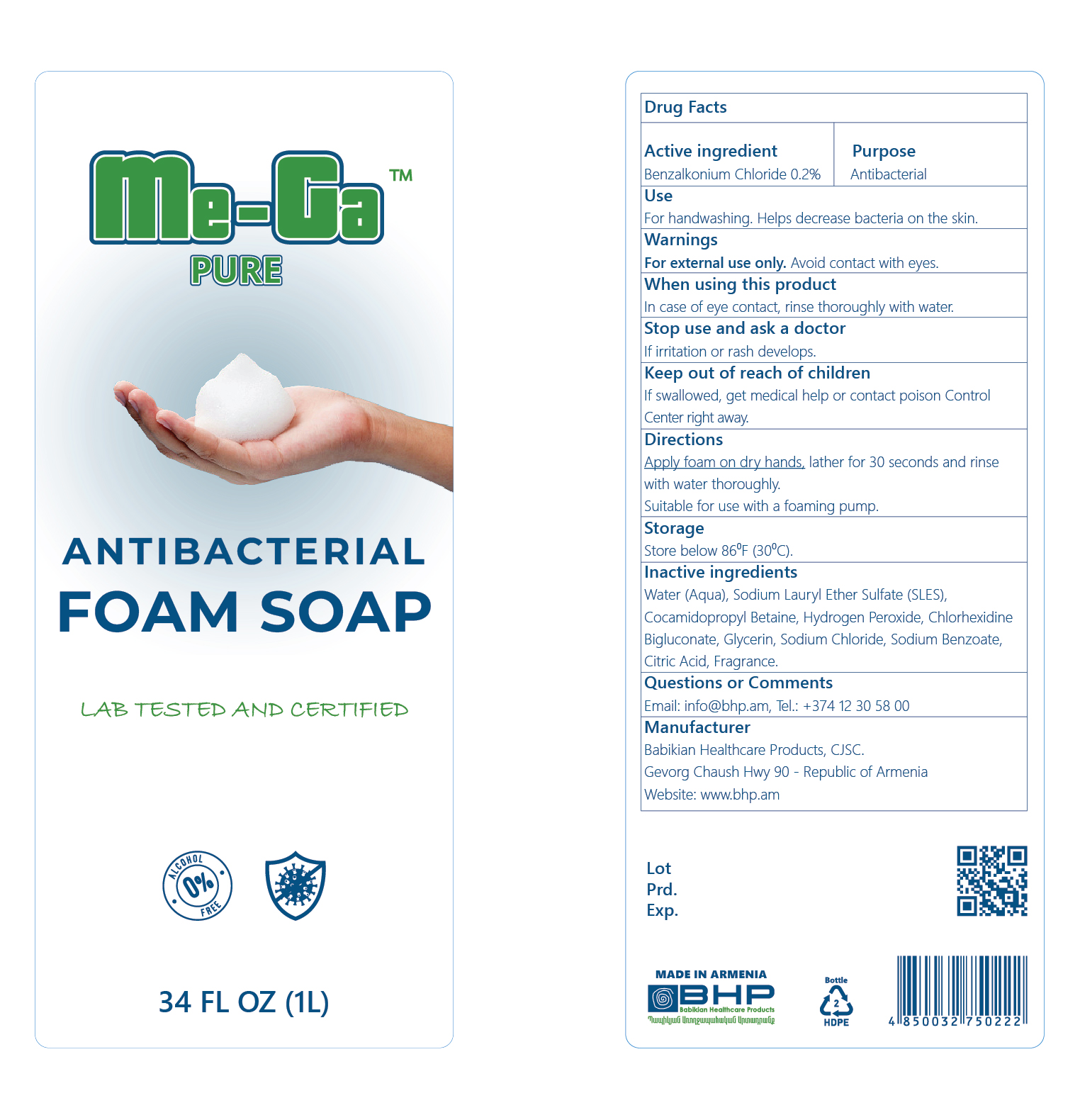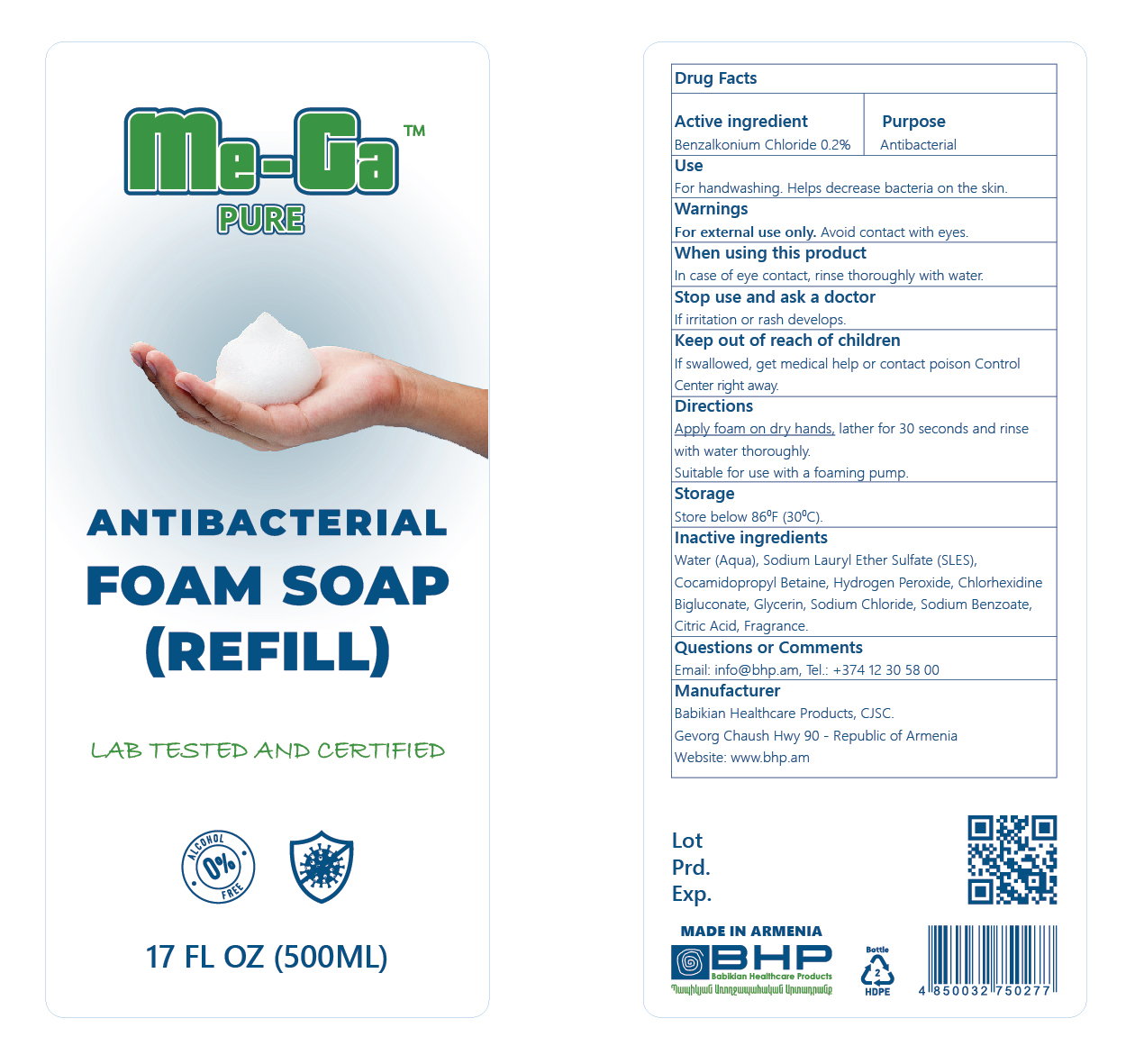 DRUG LABEL: Me-Ga Pure Antibacterial
NDC: 83640-402 | Form: SOAP
Manufacturer: Babikian Healthcare Products CJSC
Category: otc | Type: HUMAN OTC DRUG LABEL
Date: 20250507

ACTIVE INGREDIENTS: BENZALKONIUM CHLORIDE 0.2 mg/100 mL
INACTIVE INGREDIENTS: COCAMIDOPROPYL BETAINE; CHLORHEXIDINE DIGLUCONATE; SODIUM CHLORIDE; SODIUM LAURETH SULFATE; GLYCERIN; WATER; HYDROGEN PEROXIDE; SODIUM BENZOATE; CITRIC ACID

Drug Facts

Active ingredient ....................... Purpose

Benzalkonium Chloride 0.2% .... Antibacterial

Use

For handwashing. Helps decrease bacteria on the skin.

Warnings

For extrenal use only.

Avoid contact with eyes.

When using this product

In case of eye contact, rinse thoroughly with water.

Stop use and ask a doctor

If irritation or rash develops.

Keep out of reach of children

If swallowed, get medical help or contact poison Control Center right away.

Directions

Apply foam on dry hands, lather for 30 seconds and rinse with water thoroughly.

Suitable for use with a foaming pump.

Storage

Store below 86^0 F (30^0 C).

INACTIVE INGREDIENT

Water (Aqua), Sodium Lauryl Ether Sulfate (SLES), Cocamidopropyl Betaine, Hydrogen Peroxide, Chlorhexidine Bigluconate, Glycerin, Sodium Chloride, Sodium Benzoate, Citric Acid, Fragrance.

Questions or Comments

Email: info@bhp.am, Tel.: +374 12 30 58 00

Manufacturer

Babikian Healthcare Products, CJSC.

Gevorg Chaush Hwy 90 - Republic of Armenia

Website: www.bhp.am